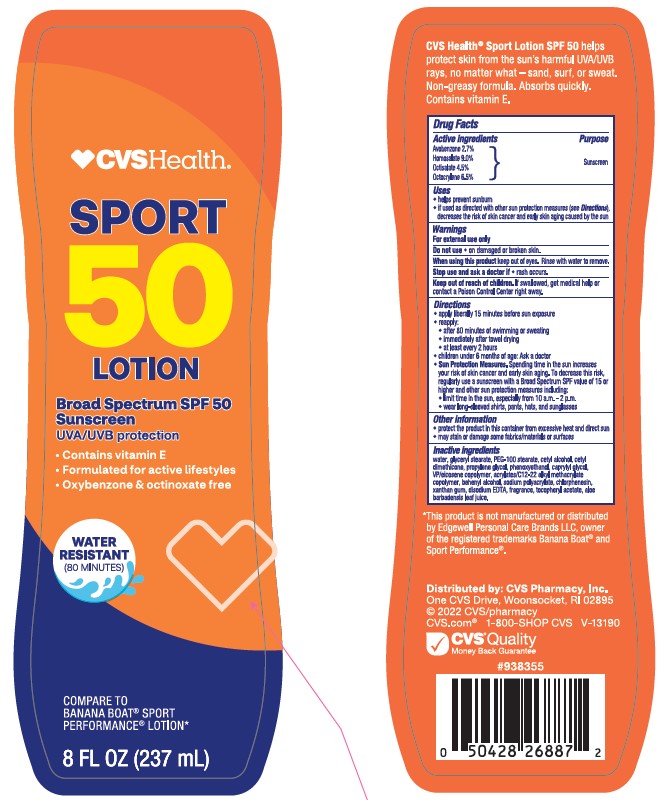 DRUG LABEL: CVS Health Sport SPF 50
NDC: 51316-037 | Form: LOTION
Manufacturer: CVS PHARMACY
Category: otc | Type: HUMAN OTC DRUG LABEL
Date: 20241017

ACTIVE INGREDIENTS: OCTOCRYLENE 65 mg/1 mL; AVOBENZONE 27 mg/1 mL; HOMOSALATE 90 mg/1 mL; OCTISALATE 45 mg/1 mL
INACTIVE INGREDIENTS: .ALPHA.-TOCOPHEROL ACETATE; EICOSYL POVIDONE; DOCOSANOL; ALOE VERA LEAF; BUTYL ACRYLATE/C16-C20 ALKYL METHACRYLATE/METHACRYLIC ACID/METHYL METHACRYLATE COPOLYMER; PEG-100 STEARATE; GLYCERYL 1-STEARATE; CETYL ALCOHOL; PROPYLENE GLYCOL; DIMETHICONE; CAPRYLYL GLYCOL; CHLORPHENESIN; EDETATE DISODIUM; CETYL DIMETHICONE 45; PHENOXYETHANOL; WATER; XANTHAN GUM; SODIUM POLYACRYLATE (8000 MW)

CVS Health Sport SPF 50 Lotion

Active ingredients

Avobenzone 2.7%

Homosalate 9.0%

Octisalate 4.5%

Octocrylene 6.5%

Purpose

Sunscreen

Uses

- helps prevent sunburn
- if used as directed with other sun protection measures (see Directions), decreases the risk of skin cancer and early skin aging caused by the sun

Warnings

For external use only

Do not use

- on damaged or broken skin

When using this product

- keep out of eyes. Rinse with water to remove.

Stop use and ask doctor if

- rash occurs.

Keep out of reach of children.

If swallowed, get medical help or contact a Poison Control Center right away.

Directions

- apply liberally 15 minutes before sun exposure

- reapply:
- after 80 minutes of swimming or sweating
- immediately after towel drying
- at least every 2 hours

- children under 6 months of age: Ask a doctor

- Sun Protection Measures. Spending time in the sun increases your risk of skin cancer and early skin aging. To decrease this risk, regularly use a sunscreen with a Broad Spectrum SPF value of 15 or higher and other sun protection measures including:
- limit time in the sun, especially from 10 a.m. - 2 p.m.
- wear long-sleeved shirts, pants, hats, and sunglasses

Other information

• protect the product in this container from excessive heat and direct sun
• may stain or damage some fabrics, materials or surfaces

Inactive ingredients

WATER, GLYCERYL STEARATE, PEG-100 STEARATE, CETYL ALCOHOL, CETYL DIMETHICONE, PROPYLENE GLYCOL, PHENOXYETHANOL, CAPRYLYL GLYCOL, VP/EICOSENE COPOLYMER, ACRYLATES/C12-22 ALKYL METHACRYLATE COPOLYMER, BEHENYL ALCOHOL, SODIUM POLYACRYLATE, CHLORPHENESIN, XANTHAN GUM, DISODIUM EDTA, FRAGRANCE, TOCOPHERYL ACETATE, ALOE BARBADENSIS LEAF JUICE